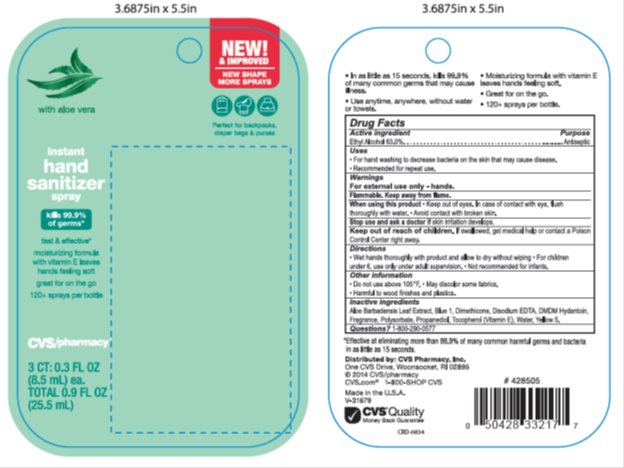 DRUG LABEL: CVS Hand Sanitizer
NDC: 69842-557 | Form: SPRAY
Manufacturer: CVS
Category: otc | Type: HUMAN OTC DRUG LABEL
Date: 20150817

ACTIVE INGREDIENTS: ALCOHOL 56 mg/1 g
INACTIVE INGREDIENTS: EDETATE DISODIUM 0.010 mg/1 g; PROPANEDIOL 1.7 mg/1 g; POLYSORBATE 20 4.46 mg/1 g; DIMETHICONE .12 mg/1 g

Drug Facts

Active ingredient

Ethyl Alcohol 63.00%

Purpose

Antiseptic

Keep Out of Reach of Children

If swallowed get medical help or contact a Poison Control Center right away.

Uses

For handwashing to decrease bacteria on the skin that may cause disease. Recommended for repeat use.

Warnings

For external use only: Hands. Flammable. Keep away from flame.

When using this product: keep out of eyes. In case of contact with eyes, flush thoroughly with water. Avoid contact with broken skin. Do not inhale or ingest. Stop use and ask a doctor: if irritation develops.

Directions

Wet hands thoroughly with product and allow to dry without wiping. For children under 6, use only under adult supervision. Not recommended for infants.

Inactive Ingredients

Aloe Barbadensis Leaf Extract, Blue 1, Dimethicone, Disodium EDTA, DMDM Hydantoin, Fragrance, Polysorbarte, Propanediol, Tocopherol (Vitamin E), Water, Yellow 5.